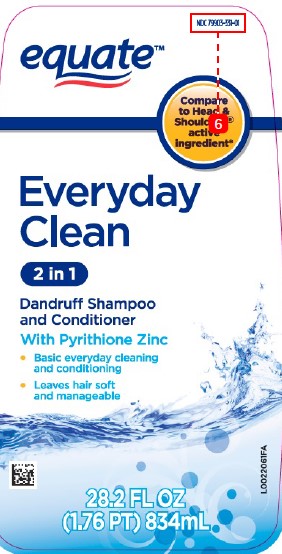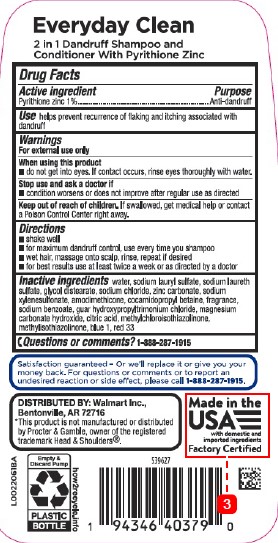 DRUG LABEL: Everyday Clean 2 in 1
NDC: 79903-331 | Form: SHAMPOO
Manufacturer: Walmart Inc.
Category: otc | Type: HUMAN OTC DRUG LABEL
Date: 20260227

ACTIVE INGREDIENTS: PYRITHIONE ZINC 10 mg/10 mL
INACTIVE INGREDIENTS: WATER; SODIUM LAURYL SULFATE; SODIUM LAURETH SULFATE; GLYCOL DISTEARATE; SODIUM CHLORIDE; ZINC CARBONATE; SODIUM XYLENESULFONATE; AMODIMETHICONE (800 CST); COCAMIDOPROPYL BETAINE; SODIUM BENZOATE; GUAR HYDROXYPROPYLTRIMONIUM CHLORIDE (1.7 SUBSTITUENTS PER SACCHARIDE); MAGNESIUM CARBONATE HYDROXIDE; CITRIC ACID MONOHYDRATE; METHYLCHLOROISOTHIAZOLINONE; METHYLISOTHIAZOLINONE; FD&C BLUE NO. 1; D&C RED NO. 33

Equate 311.007/311 AK-AN
Everyday Clean 2 in 1 Dandruff Shampoo

Claims

Everyday Clean

2 in 1 Dandruff Shampoo and

Conditioner With Pyrithione Zinc

Active ingredients

Pyrithione zinc 1%

Purpose

Anti-dandruff

Use

Helps prevent recurrence of flaking and itching associated with dandruff

Warnings

For external use only

When using this product

- do not get into eyes. If contact occurs, rinse eyes thoroughly with water

Stop use and ask a doctor if

- condition worsens or does not improve after regular use as directed

Keep out of reach of children

If swallowed, get medical help or contact a Poison Control Center Right away.

Directions

- Shake well
- for maximum dandruff control, use every time you shampoo
- wet hair, massage onto scalp, rinse, repeat if desired
- for best results use at least twice a week or as directed by a doctor

inactive ingredients

water, sodium lauryl sulfate, sodium laureth sulfate, glycol distearate, sodium chloride, zinc carbonate, sodium xylenesulfonate, amodimethicone, cocamidopropyl betaine, fragrance, sodium benzoate, guar hydroxypropyltrimonium chloride, magnesium carbonate hydroxide, citric acid, methylchloroisothiazolinone, methylisothiazolinone, blue 1, red 33

ADVERSE REACTION

Satisfaction guaranteed - Or we'll replace it or give you your money back. For questions or comments or to report an undesired reaction or side effect, please call 1-888-287-1915.

DISTRIBUTED BY: Walmart Inc.,

Bentonville, AR 72716

*This product is not manufactured or distributed be Procter & Gamble, owner of the registered trademark Head & SHoulders®.

Made in the USA with domestic and imported ingredients

Factory Certified

Empty & Discard Pump

PLASTIC BOTTLE

how2recycle.info

PRINCIPAL DISPLAY PANEL

NDC 79903-331-01

equate™

Compare to Head & Shoulders® active ingredient*

Everyday

Clean

2 in 1

Dandruff Shampoo

and Conditioner

With Pyrithione Zinc

- Basic everyday cleaning and conditioning
- Leaves hair soft and manageable

28.2 FL OZ (1.76 PT) 834 mL